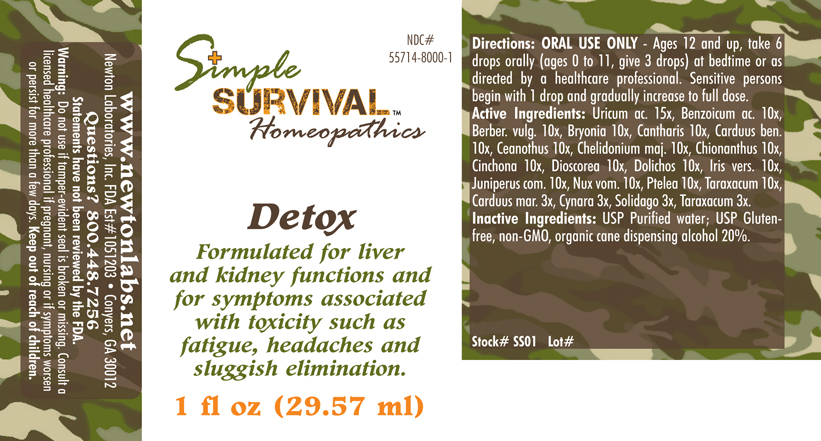 DRUG LABEL: Detox 
NDC: 55714-8000 | Form: LIQUID
Manufacturer: Newton Laboratories, Inc.
Category: homeopathic | Type: HUMAN OTC DRUG LABEL
Date: 20140415

ACTIVE INGREDIENTS: Uric Acid 15 [hp_X]/1 mL; Benzoic Acid 10 [hp_X]/1 mL; Berberis Vulgaris Root Bark 10 [hp_X]/1 mL; Bryonia Alba Root 10 [hp_X]/1 mL; Lytta Vesicatoria 10 [hp_X]/1 mL; Centaurea Benedicta 10 [hp_X]/1 mL; Ceanothus Americanus Leaf 10 [hp_X]/1 mL; Chelidonium Majus 10 [hp_X]/1 mL; Chionanthus Virginicus Bark 10 [hp_X]/1 mL; Cinchona Officinalis Bark 10 [hp_X]/1 mL; Dioscorea Villosa Tuber 10 [hp_X]/1 mL; Mucuna Pruriens Fruit Trichome 10 [hp_X]/1 mL; Iris Versicolor Root 10 [hp_X]/1 mL; Juniper Berry 10 [hp_X]/1 mL; Strychnos Nux-vomica Seed 10 [hp_X]/1 mL; Ptelea Trifoliata Bark 10 [hp_X]/1 mL; Taraxacum Officinale 10 [hp_X]/1 mL; Silybum Marianum Seed 3 [hp_X]/1 mL; Cynara Scolymus Leaf 3 [hp_X]/1 mL; Solidago Virgaurea Flowering Top 3 [hp_X]/1 mL
INACTIVE INGREDIENTS: Alcohol

Detox

INDICATIONS & USAGE SECTION

Detox Formulated for liver and kidney functions and for symptoms associated with toxicity such as fatigue, headaches and sluggish elimination.

DOSAGE & ADMINISTRATION SECTION

Directions: ORAL USE ONLY - Ages 12 and up, take 6 drops orally (ages 0 to 11, give 3 drops) at bedtime or as directed by a healthcare professional. Sensitive persons begin with 1 drop and gradually increase to full dose.

OTC - ACTIVE INGREDIENT SECTION

Uricum ac. 15x, Benzoicum ac. 10x, Berber. vulg. 10x, Bryonia 10x, Cantharis 10x, Carduus ben. 10x, Ceanothus 10x, Chelidonium maj. 10x, Chionanthus 10x, Cinchona 10x, Dioscorea 10x, Dolichos 10x, Iris vers. 10x, Juniperus com. 10x, Nux vom. 10x, Ptelea 10x, Taraxacum 10x, Carduus mar. 3x, Cynara 3x, Solidago 3x, Taraxacum 3x.

OTC - PURPOSE SECTION

Formulated for liver and kidney functions and for symptoms associated with toxicity such as fatigue, headaches and sluggish elimination.

INACTIVE INGREDIENT SECTION

Inactive Ingredients: USP Purified Water; USP Gluten-free, non-GMO, organic cane dispensing alcohol 20%

QUESTIONS SECTION

www.newtonlabs.net Newton Laboratories, Inc. FDA Est # 1051203 - Conyers, GA 30012
Questions? 1.800.448.7256

WARNINGS SECTION

Warning: Do not use if tamper - evident seal is broken or missing. Consult a licensed healthcare professional if pregnant, nursing or if symptoms worsen or persist for more than a few days. Keep out of reach of children

OTC - PREGNANCY OR BREAST FEEDING SECTION

Consult a licensed healthcare professional if pregnant, nursing or if symptoms worsen or persist for more than a few days.

OTC - KEEP OUT OF REACH OF CHILDREN SECTION

Keep out of reach of children.